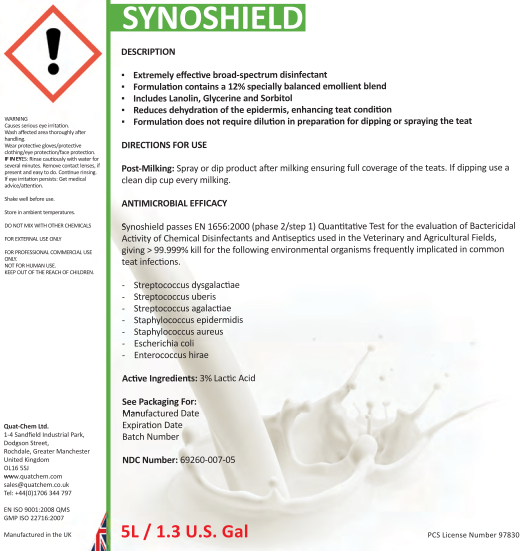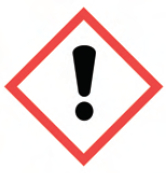 DRUG LABEL: Synoshield
NDC: 69260-011 | Form: LIQUID
Manufacturer: Quat-Chem Ltd.
Category: animal | Type: OTC ANIMAL DRUG LABEL
Date: 20160317

ACTIVE INGREDIENTS: LACTIC ACID 70 g/1 L

Synoshield

Synoshield

WARNING
Causes serious eye irritation.
Wash affected area thoroughly after handling.
Wear protective gloves/protective clothing/eye protection/face protection.
IF IN EYES: Rinse cautiously with water for several minutes. Remove contact lenses, if present and easy to do. Continue rinsing.
If eye irritation persists: Get medical advice/attention.

Shake well before use.
Store in ambient temperatures.

DO NOT MIX WITH OTHER CHEMICALS
FOR EXTERNAL USE ONLY
FOR PROFESSIONAL COMMERCIAL USE ONLY.
NOT FOR HUMAN USE.
KEEP OUT OF THE REACH OF CHILDREN

Quat-Chem Ltd.
1-4 Sandfield Industrial Park,
Dodgson Street,
Rochdale, Greater Manchester
United Kingdom
OL16 5SJ
www.quatchem.com
sales@quatchem.co.uk
Tel: +44(0)1706 344 797
EN ISO 9001:2008 QMS
GMP ISO 22716:2007
Manufactured in the UK

DESCRIPTION
▪ Extremely effective broad-spectrum disinfectant
▪ Formulation contains a 12% specially balanced emollient blend
▪ Includes Lanolin, Glycerine and Sorbitol
▪ Reduces dehydration of the epidermis, enhancing teat condition
▪ Formulation does not require dilution in preparation for dipping or spraying the teat

DIRECTIONS FOR USE
Post-Milking: Spray or dip product after milking ensuring full coverage of the teats. If dipping use a clean dip cup every milking.

ANTIMICROBIAL EFFICACY
Synoshield passes EN 1656:2000 (phase 2/step 1) Quantitative Test for the evaluation of Bactericidal Activity of Chemical Disinfectants and Antiseptics used in the Veterinary and Agricultural Fields, giving > 99.999% kill for the following environmental organisms frequently implicated in common teat infections.
- Streptococcus dysgalactiae
- Streptococcus uberis
- Streptococcus agalactiae
- Staphylococcus epidermidis
- Staphylococcus aureus
- Escherichia coli
- Enterococcus hirae

Active Ingredients: 3% Lactic Acid

See Packaging For:
Manu Manufactured Date
Expiration Date
Batch Number

NDC Number: